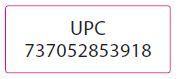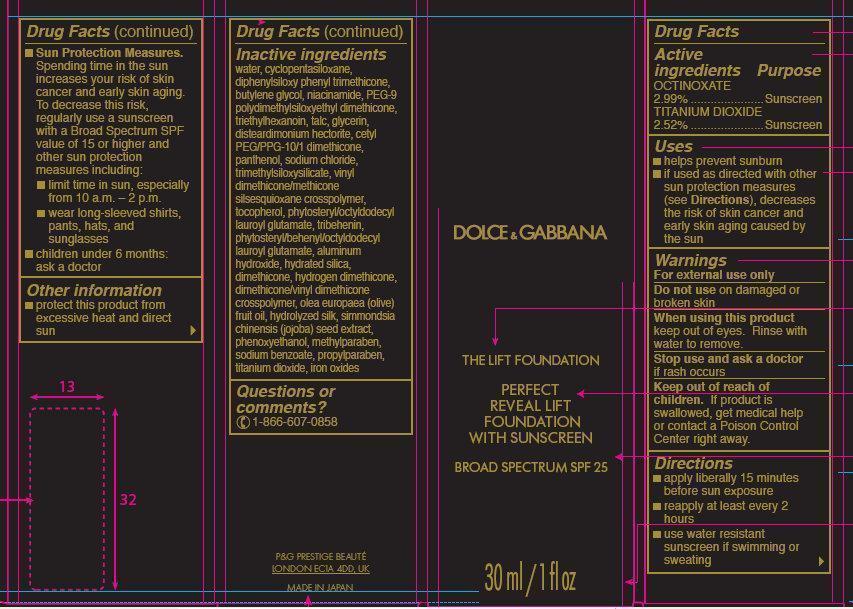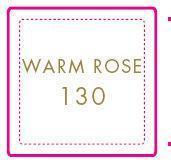 DRUG LABEL: Dolce and Gabbana The Lift Foundation Warm Rose 130
NDC: 37000-914 | Form: LIQUID
Manufacturer: Proter & Gamble Manufacturing Company
Category: otc | Type: HUMAN OTC DRUG LABEL
Date: 20171221

ACTIVE INGREDIENTS: OCTINOXATE 29.9 mg/1 mL; TITANIUM DIOXIDE 25.2 mg/1 mL
INACTIVE INGREDIENTS: WATER; CYCLOMETHICONE 5; DIPHENYLSILOXY PHENYL TRIMETHICONE; BUTYLENE GLYCOL; NIACINAMIDE; PEG-9 POLYDIMETHYLSILOXYETHYL DIMETHICONE; TRIETHYLHEXANOIN; TALC; GLYCERIN; DISTEARDIMONIUM HECTORITE; PANTHENOL; SODIUM CHLORIDE; TOCOPHEROL; TRIBEHENIN; ALUMINUM HYDROXIDE; HYDRATED SILICA; DIMETHICONE; OLIVE OIL; SIMMONDSIA CHINENSIS SEED; PHENOXYETHANOL; METHYLPARABEN; SODIUM BENZOATE; PROPYLPARABEN; FERRIC OXIDE RED

Dolce and Gabbana The Lift Foundation Warm Rose 130

Active ingredients

OCTINOXATE 2.99%
TITANIUM DIOXIDE 2.52%

Purpose

Sunscreen

Uses

- helps prevent sunburn
- if used as directed with other sun protection measures (see Directions), decreases the risk of skin cancer and early skin aging caused by the sun

Warnings

For external use only

Do not use

on damaged or broken skin

When using this product

keep out of eyes. Rinse with water to remove.

Stop use and ask a doctor

if rash occurs

Keep out of reach of children.

If product is swallowed, get medical help or contact a Poison Control Center right away.

Directions

- apply liberally 15 minutes before sun exposure
- reapply at least every 2 hours
- use water resistant sunscreen if swimming or sweating
- Sun Protection Measures. increases your risk of skin cancer and early skin aging. To decrease this risk, regularly use a sunscreen with a Broad Spectrum SPF value of 15 or higher and other sun protection measures including:
-
  - limit time in sun, especially from 10 a.m. – 2 p.m.
  - wear long-sleeved shirts, pants, hats, and sunglasses
- children under 6 months: ask a doctor

Other information

- protect this product from excessive heat and direct sun

Inactive ingredients

water, cyclopentasiloxane, diphenylsiloxy phenyl trimethicone, butylene glycol, niacinamide, PEG-9 polydimethylsiloxyethyl dimethicone, triethylhexanoin, talc, glycerin, disteardimonium hectorite, cetyl PEG/PPG-10/1 dimethicone, panthenol, sodium chloride, trimethylsiloxysilicate, vinyl dimethicone/methicone silsesquioxane crosspolymer, tocopherol, phytosteryl/octyldodecyl lauroyl glutamate, tribehenin, phytosteryl/behenyl/octyldodecyl lauroyl glutamate, aluminum hydroxide, hydrated silica, dimethicone, hydrogen dimethicone, dimethicone/vinyl dimethicone crosspolymer, olea europaea (olive) fruit oil, hydrolyzed silk, simmondsia chinensis (jojoba) seed extract, phenoxyethanol, methylparaben, sodium benzoate, propylparaben, titanium dioxide, iron oxides

Questions or comments?

1-866-607-0858

PACKAGE LABEL

DOLCE AND GABBANA

THE LIFT FOUNDATION

PERFECT
REVEAL LIFT
FOUNDATION
WITH SUNSCREEN

BROAD SPECTRUM SPF 25

30ml / 1 fl oz

P&G PRESTIGE BEAUTE
LONDON ECIA 4DD, UK

MADE IN JAPAN

WARM ROSE 130